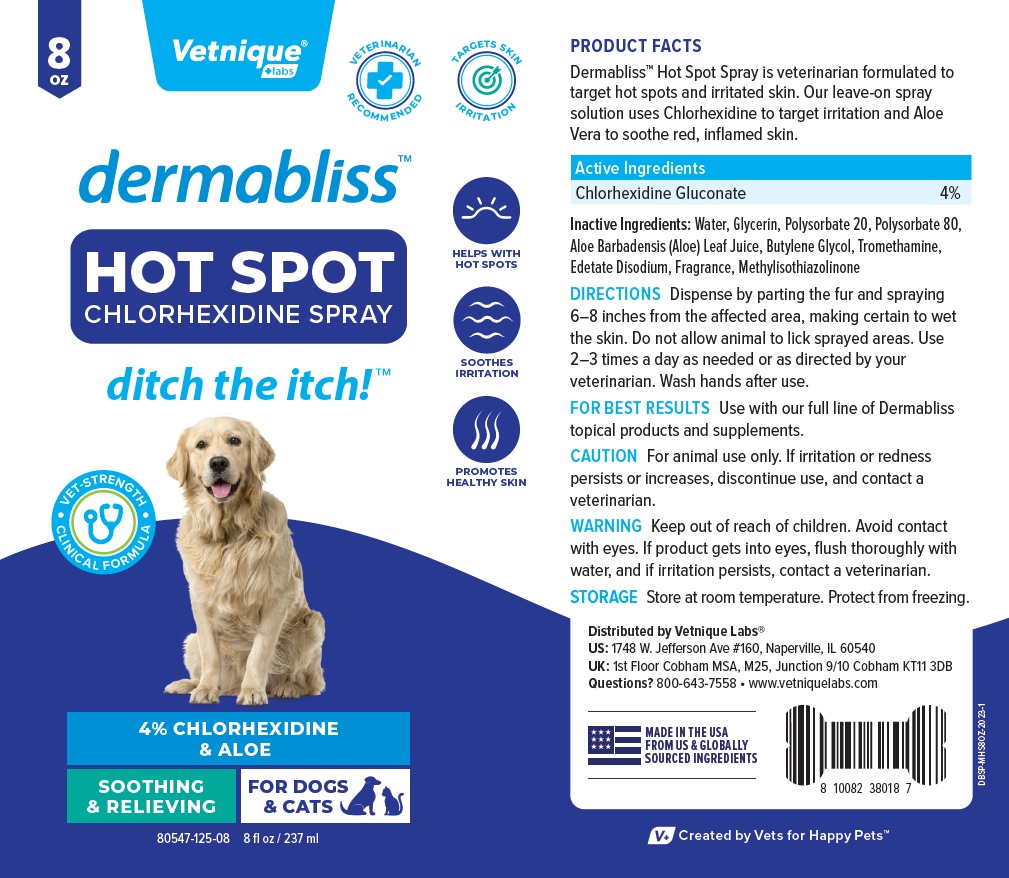 DRUG LABEL: dermabliss HOT SPOT
NDC: 80547-125 | Form: SPRAY
Manufacturer: Vetnique Labs LLC
Category: animal | Type: OTC ANIMAL DRUG LABEL
Date: 20231005

ACTIVE INGREDIENTS: CHLORHEXIDINE GLUCONATE 40 mg/1 mL
INACTIVE INGREDIENTS: WATER; GLYCERIN; POLYSORBATE 20; POLYSORBATE 80; ALOE VERA LEAF; BUTYLENE GLYCOL; TROMETHAMINE; EDETATE DISODIUM; METHYLISOTHIAZOLINONE

dermablissTM HOT SPOT CHLORHEXIDINE SPRAY

PRODUCT FACTS

Dermabliss™ Hot Spot Spray is veterinarian formulated to target hot spots and irritated skin. Our leave-on spray solution uses Chlorhexidine to target irritation and Aloe Vera to soothe red, inflamed skin.

Active Ingredients

Chlorhexidine Gluconate 4%

Inactive Ingredients:

Water, Glycerin, Polysorbate 20, Polysorbate 80, Aloe Barbadensis (Aloe) Leaf Juice, Butylene Glycol, Tromethamine, Edetate Disodium, Fragrance, Methylisothiazolinone

DIRECTIONS

Dispense by parting the fur and spraying 6-8 inches from the affected area, making certain to wet the skin. Do not allow animal to lick sprayed areas. Use 2-3 times a day as needed or as directed by your veterinarian. Wash hands after use.

FOR BEST RESULTS Use with our full line of Dermabliss topical products and supplements.

CAUTION

For animal use only. If irritation or redness persists or increases, discontinue use, and contact a veterinarian.

WARNING

Keep out of reach of children. Avoid contact with eyes. If product gets into eyes, flush thoroughly with water, and if irritation persists, contact a veterinarian.

STORAGE

Store at room temperature. Protect from freezing.

Questions?

800-643-7558 • www.vetniquelabs.com

VETERINARIAN RECOMMENDED

TARGETS SKIN IRRITATION

ditch the itch!™

HELPS WITH HOT SPOTS

SOOTHES IRRITATION

PROMOTES HEALTHY SKIN

VET-STRENGTH CLINICAL FORMULA

SOOTHING & RELIEVING

FOR DOGS & CATS

Distributed by Vetnique Labs®
US: 1748 W. Jefferson Ave#160, Naperville, IL 60540
UK: 1st Floor Cobham MSA, M25, Junction 9/10 Cobham KT11 3DB

MADE IN THE USA
FROM US & GLOBALLY SOURCED INGREDIENTS

V+ Created by Vets for Happy Pets™